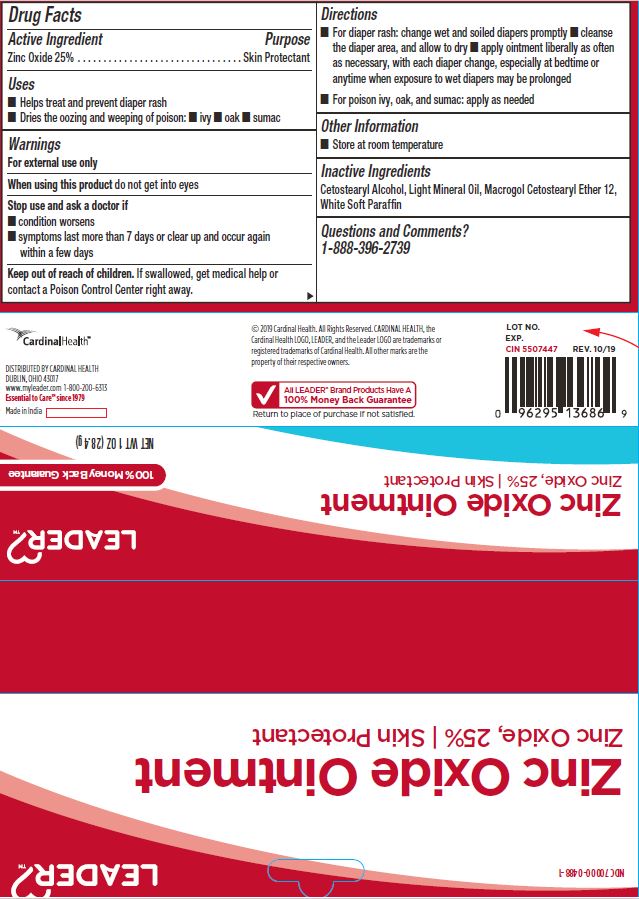 DRUG LABEL: Skin Protectant
NDC: 70000-0488 | Form: OINTMENT
Manufacturer: Cardinal Health
Category: otc | Type: HUMAN OTC DRUG LABEL
Date: 20251125

ACTIVE INGREDIENTS: ZINC OXIDE 25 mg/100 mg
INACTIVE INGREDIENTS: CETEARETH-12; CETOSTEARYL ALCOHOL; LIGHT MINERAL OIL; PETROLATUM

CR-1190 Zinc Oxide 25% Skin Protectant NDC 70000-0488-1

Active Ingredient

Zinc Oxide 25%

Purpose

Skin Protectant

Uses

- Helps treat and prevent diaper rash
- Dries the oozing and weeping of poison: ivy, oak, sumac

Warnings

For external use only

When using this product

do not get into eyes

Stop use and ask a doctor if

- condition worsens
- symptoms last more than 7 days or clear up and occur again within a few days

KEEP OUT OF REACH OF CHILDREN

If swallowed, get medical help or contact a Poison Control Center right away.

Directions

- For diaper rash: change wet and soiled diapers promptly, cleanse the diaper area and allow to dry, apply ointment liberally as often as necessary, with each diaper change, especially at bedtime or anytime when exposure to wet diapers may be prolonged.
  - for poison ivy, oak, and sumac: apply as needed.

Other Information

Store at room temperature

Inactive Ingredients

Cetostearyl Alcohol, Light Mineral Oil, Macrogol Cetostearyl Ether 12, White Soft Paraffin

Questions and Comments?

1-888-396-2739